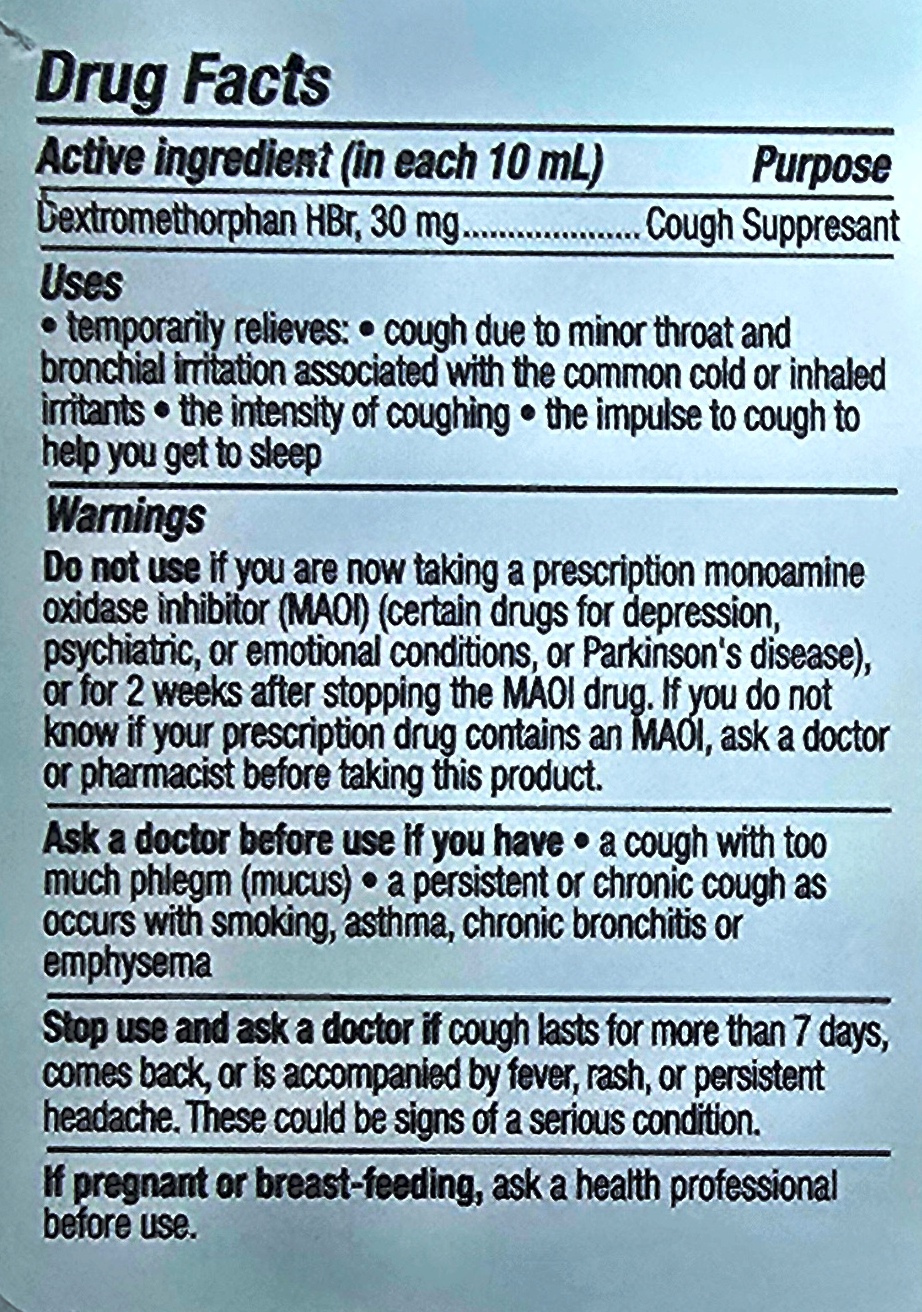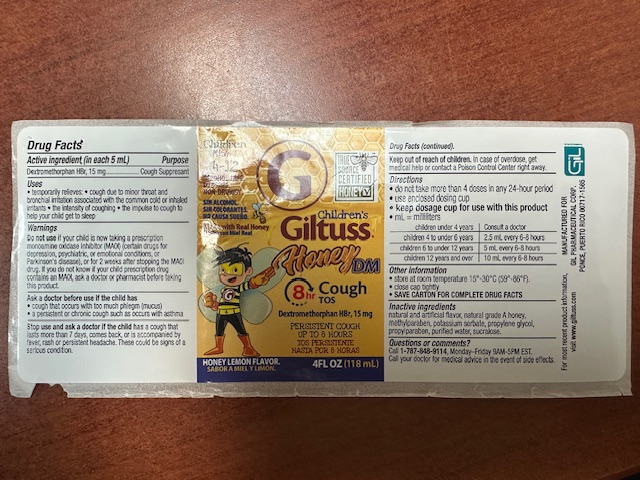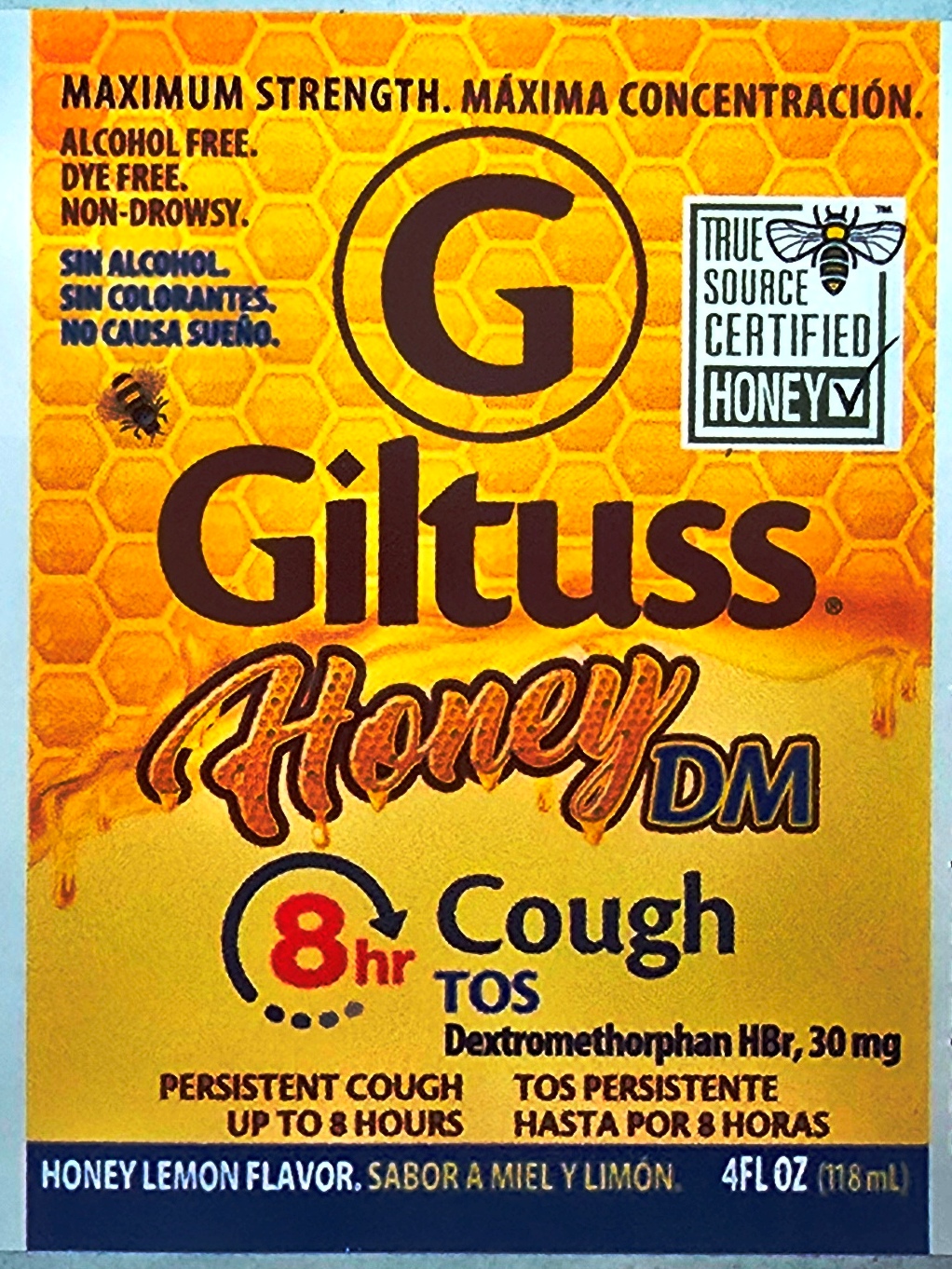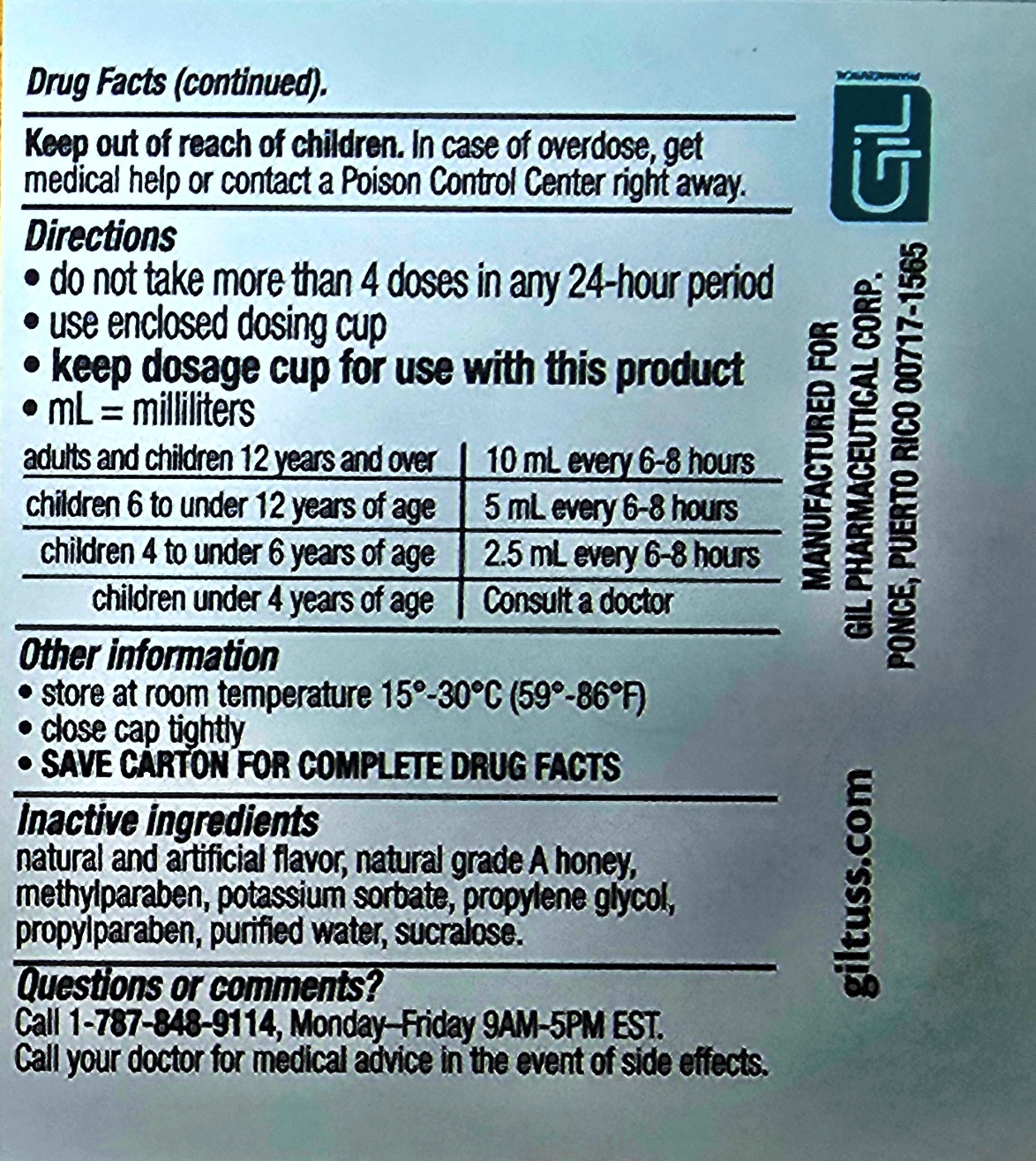 DRUG LABEL: Giltuss Honey DM Cough
NDC: 65852-004 | Form: SOLUTION
Manufacturer: Dextrum Laboratories, Inc
Category: otc | Type: HUMAN OTC DRUG LABEL
Date: 20250923

ACTIVE INGREDIENTS: DEXTROMETHORPHAN HYDROBROMIDE 30 mg/10 mL
INACTIVE INGREDIENTS: PROPYLPARABEN; PROPYLENE GLYCOL; HONEY; METHYLPARABEN; SUCRALOSE; WATER; POTASSIUM SORBATE

Giltuss Honey DM Cough

Active Ingredients

Active Ingredients (in each 10 ml)

Dextromethorphan, 30 mg

Purpose and uses

Purpose

Cough supresant

Uses

Temporary relieves:

Cough due to minor throat and bronchial irritation associated with the common cold or inhaled irritants, the intensity of coughing ,the impulse to cough to help you get sleep,

Warning

Warnings

Do not use

If you are taking a prescription monoamine oxidase inhibitor (MAOI) (certains drugs for depression, psychiatric, or emotional conditions, or Parkinson's disease), or for 2 weeks after stopping the MAOI drug. If you dont know is your prescription drug contains and MAOI, ask a doctor or pharmacist before taking this product.

Ask a doctor before use if you have, a cough with too much phlegm (mucus) , a persistent or chronic cough as occurs with smoking, asthma, chronic bronchitis, or emphysema.

Stop use

Stop use and ask a doctor if

cough lasts for more than 7 days , come back, or is accompanied by fever, rash or persistent headache. These could be signs of serious condition.

If Pregnant

If pregnant or breast- feeding, ask a health professional before use. Keep out of reach of children.

In case of accidental overdose, get medical or professional help or contact a Poisson Control center immediately

Indication and usage section

Do not take more than 4 doses in any 24 hours period

Use enclosed dosing cup

Keep dosing cup for use with this product

ml= mililiters

Adults and children 12 years & over 10 ml every 6-8 hours

children 6 to under 12 years of age 5 ml every 6-8 hours

children 4 to under 6 years of age 2.5 ml every 6-8 hours

children under 4 years of age Consult a doctor

Other information

Store at room temperature 15-30 °C (59° -86 ° F)
Close cap tightly
SAVE CARTON FOR COMPLETE DRUG FACTS

Inactive ingredients

natural and artificial flavor, natural grade A honey, methylparaben, potassium sorbate, propylene glycol, propylparaben, purified water, sucralose

Dosage

Dosage and administration

Do not take more than 4 doses in any 24 hours period

Use enclosed dosing cup

Keep dosing cup for use with this product

ml= mililiters

Adults and children 12 years & over 10 ml every 6-8 hours

children 6 to under 12 years of age 5 ml every 6-8 hours

children 4 to under 6 years of age 2.5 ml every 6-8

Keeo out of the reach of children.

in case of overdose, get medical help or contact a Poison Control Center right away.

Principal panel

Maximum strength

Alcohol free, dye free, Non-Drowsy

The source Cerified Honey

Giltus Honey DM

Cough

Dextromethorphan HBr, 30 mg

Persistent Cough

Up to 8 hours

Honey lemon flavor

4 floz 118 ml